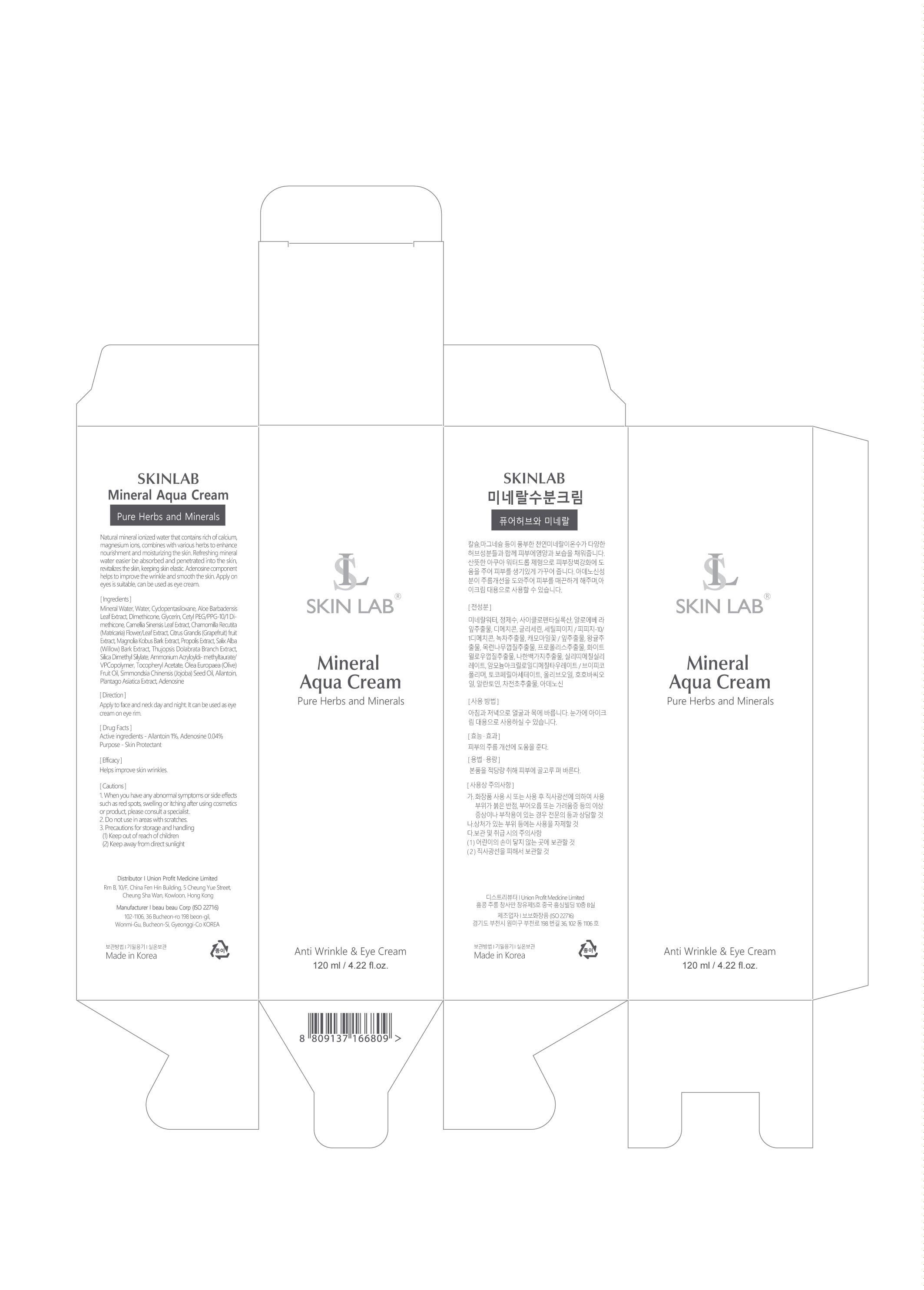 DRUG LABEL: Mineral Aqua Cream
NDC: 73101-002 | Form: LIQUID
Manufacturer: UNION PROFIT MEDICINE LIMITED
Category: otc | Type: HUMAN OTC DRUG LABEL
Date: 20200518

ACTIVE INGREDIENTS: ALLANTOIN 1 g/100 g
INACTIVE INGREDIENTS: WATER

Direction

Apply to face and neck day and night. it can be used as eye cream on eye rim

Caution

1.When you have any abnormal symptoms or side effects such as red spots,swelling or itching after using after using cosmetics or product, please consult a specialist

2.Do not use in areas with scratches

3. Precautions for storage and handing

-Keep out of reach of children.

-Keep at room temperature and avoid direct sunlight.

INDICATIONS AND USAGE

helps improve skin wrinks

Keep out of reach of children.

PURPOSE

helps improve skin wrinkles

drug fact

Active ingredients-allantoin 1%,Adenosine 0.04%